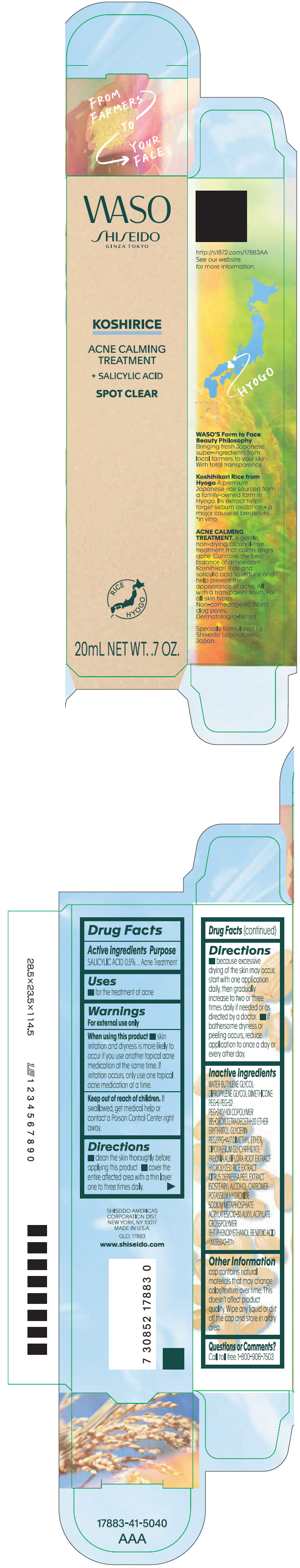 DRUG LABEL: SHISEIDO WASO KOSHIRICE ACNE CALMING TREATMENT
NDC: 58411-615 | Form: GEL
Manufacturer: SHISEIDO AMERICAS CORPORATION
Category: otc | Type: HUMAN OTC DRUG LABEL
Date: 20260105

ACTIVE INGREDIENTS: SALICYLIC ACID 0.1 g/20 mL
INACTIVE INGREDIENTS: WATER; DIPROPYLENE GLYCOL; BUTYLENE GLYCOL; DIMETHICONE; POLYETHYLENE GLYCOL 300; POLYETHYLENE GLYCOL 1600; GLYCERIN; ERYTHRITOL; PHENOXYETHANOL; ISOSTEARYL ALCOHOL; CARBOMER HOMOPOLYMER, UNSPECIFIED TYPE; POTASSIUM HYDROXIDE; PEG/PPG-14/7 DIMETHYL ETHER; GLYCYRRHIZINATE DIPOTASSIUM; CARBOMER INTERPOLYMER TYPE A (ALLYL SUCROSE CROSSLINKED); SODIUM POLYMETAPHOSPHATE; PAEONIA LACTIFLORA ROOT; TANGERINE PEEL; BUTYLATED HYDROXYTOLUENE; BENZOIC ACID

SHISEIDO WASO KOSHIRICE ACNE CALMING TREATMENT

Drug Facts

Active ingredients

SALICYLIC ACID 0.5%

Purpose

Acne medication

Uses

- For the treatment of acne

Warnings

For external use only

When using this product

- skin irritation and dryness is more likely to occur if you use another topical acne medication at the same time. If irritation occurs, only use one topical acne medication at a time.

Keep out of reach of children.

- If swallowed, get medical help or contact a Poison Control Center right away.

Directions

- clean the skin thoroughly before applying this product.
- cover the entire affected area with a thin layer one to three times daily.
- because excessive drying of the skin may occur, start with one application daily, then gradually increase to two or three times daily if needed or as directed by a doctor.
- if bothersome dryness or peeling occurs, reduce application to once a day or every other day.

Inactive Ingredients

WATER▪BUTYLENE GLYCOL▪DIPROPYLENE GLYCOL▪DIMETHICONE▪PEG-6▪PEG-32▪PEG-240/HDI COPOLYMER BIS-DECYLTETRADECETH-20 ETHER▪ERYTHRITOL▪GLYCERIN▪PEG/PPG-14/7 DIMETHYL ETHER▪DIPOTASSIUM GLYCYRRHIZATE▪PAEONIA ALBIFLORA ROOT EXTRACT▪HYDROLYZED RICE EXTRACT▪CITRUS DEPRESSA PEEL EXTRACT▪ISOSTEARYL ALCOHOL▪CARBOMER▪POTASSIUM HYDROXIDE▪SODIUM METAPHOSPHATE▪ACRYLATES/C10-30 ALKYL ACRYLATE CROSSPOLYMER▪BHT▪PHENOXYETHANOL▪BENZOIC ACID▪ <M095042-811>

Other information

cap contains natural materials that may change color/texture over time. This doesn't affect product quality. Wipe any liquid or dirt off the cap and store in a dry area.

Questions or comments?

Call toll free 1-800-906-7503

PRINCIPAL DISPLAY PANEL - 20 mL Tube Carton

WASO
SHISEIDO
GINZA TOKYO

KOSHIRICE

ACNE CALMING
TREATMENT

+ SALICYLIC ACID

SPOT CLEAR

RICE
HYOGO

20mL NET WT. .7 OZ.